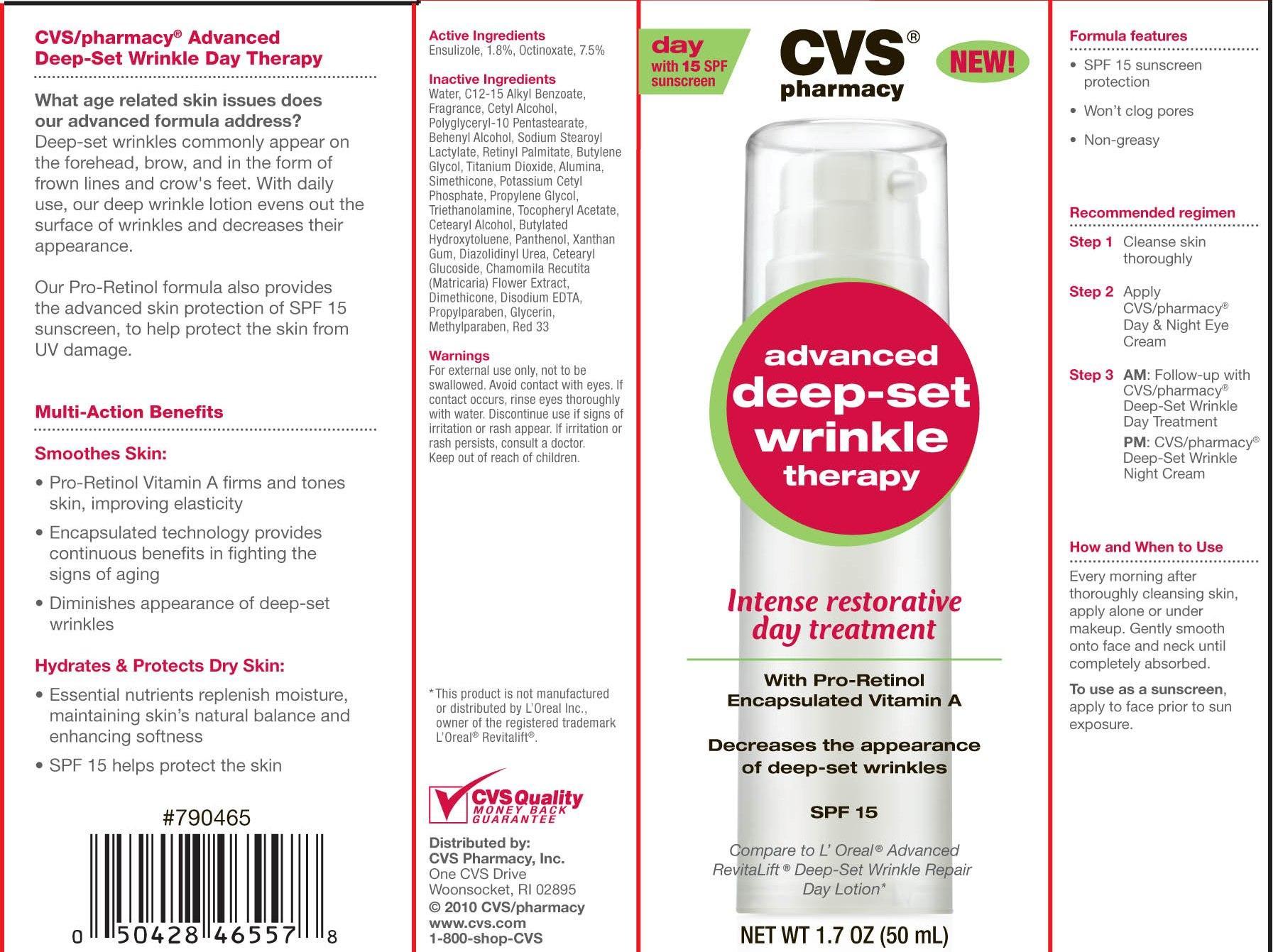 DRUG LABEL: CVS Advanced Deep Set Wrinkle Therapy w/SPF15
NDC: 59779-063 | Form: LOTION
Manufacturer: CVS Pharmacy
Category: otc | Type: HUMAN OTC DRUG LABEL
Date: 20110719

ACTIVE INGREDIENTS: ENSULIZOLE 18 mg/1 mL; OCTINOXATE 75 mg/1 mL
INACTIVE INGREDIENTS: WATER; GLYCERIN; EDETATE DISODIUM; XANTHAN GUM; TITANIUM DIOXIDE; BUTYLENE GLYCOL; ALUMINUM OXIDE; DIMETHICONE; STEARYL ALCOHOL; TROLAMINE; CETYL ALCOHOL; SODIUM STEAROYL LACTYLATE; DOCOSANOL; .ALPHA.-TOCOPHEROL ACETATE; VITAMIN A PALMITATE; CETOSTEARYL ALCOHOL; PANTHENOL; CETEARYL GLUCOSIDE; PROPYLPARABEN; METHYLPARABEN; DIAZOLIDINYL UREA; BUTYLATED HYDROXYTOLUENE; POTASSIUM CETYL PHOSPHATE; CHAMAEMELUM NOBILE FLOWER; STEARIC ACID; ALKYL (C12-15) BENZOATE; D&C RED NO. 33

drug facts

Active Ingredients:
Ensulizole, 1.8%, Octinoxate, 7.5%

PURPOSE

CVS/pharmacy Advanced Deep-Set Wrinkle Day Therapy
What age related skin issues does our advanced formula address?
Deep-set wrinkles commonly appear on the forehead, brow and in the form
of frown lines and crow's feet. With daily use, our deep wrinkle lotion evens out the
surface of wrinkles and decreases their appearance.
Our Pro-Retinol formula also provides the advanced skin protection of SPF 15 sunscreen
to help protect the skin from UV damage.
Multi-Action Benefits
Smooths Skin:
- Pro-Retinol Vitamin A firms and tones skin, improving elasticity.
- Encapsulated technology provides continuous benefits in fighting the
signs of aging
- Diminishes appearance of deep-set wrinkles.
Hydrates and Protects Dry Skin:
- Essential nutrients replenish moisture, maintaining skin's natural balance and
enhancing softness
- SPF 15 helps protect the skin

Keep out of reach of children.

INDICATIONS AND USAGE

Recomended regimen
Step 1 Cleanse skin thoroughly
Step 2 Apply CVS/pharmacy Day and Night Eye Cream
Step 3 AM: Follow-up with CVS/pharmacy Deep-Set Wrinkle Day Treatment.
PM: CVS/pharmacy Deep-Set Wrinkle Night Cream.
How and When to Use
Every morning after thoroughly cleansing skin, apply alone or under makeup.
Gently smooth onto face and neck until completely absorbed.
To use as a sunscreen apply to face prior to sun exposure

Warnings
For external use only, not to be swallowed. Avoid contact with eyes.
If contact occurs, rinse eyes thoroughly with water. Discontinue use if signs of irritation
or rash appear. If irritation or rash persists, consult a doctor.
Keep out of reach of children.

DOSAGE AND ADMINISTRATION

Recommended Application
Step 1 Cleanse skin thoroughly
Step 2 Apply CVS/Pharmacy Day and NIght Cream
Step 3 AM: Follow-up with CVS?Pharmacy Advanced Anti-Wrinkle and Firming Day Cream
PM: Follow-up with CVS/Pharmacy Advanced Anti-Wrinkle and Firming Night Cream
How and When to Use
Every day prior to sun exposure, gently smooth onto face and neck until completely absorbed. Use in the morning; alone or under makeup.
To use as a sunscreen, apply to face prior to sun exposure.

Inactive Ingredients
Water, C12-15 Alkyl Benzoate, Fragrance, Cetyl Alcohol, PolyGlyceryl-10 Pentastearate,
Behenyl Alcohol, Sodium Stearoyl Lactylate, Retinyl Palmitate, Butylene Glycol,
Titanium Dioxide, Alumina, Simethicone, Potassium Cetyl Phosphate, Propylene Glycol,
Triethanolamine, Tocopheryl Acetate, Cetearyl Alcohol, Butylated Hydroxytoluene, Panthenol,
Xanthan Gum, Diazolidinyl Urea, Cetearyl Glocoside, Chamomila Recutita (Matricaria) Flower
Extract, Dimethicone, Disodium EDTA, Propylparaben, Glycerin, Methylparaben, Red 33